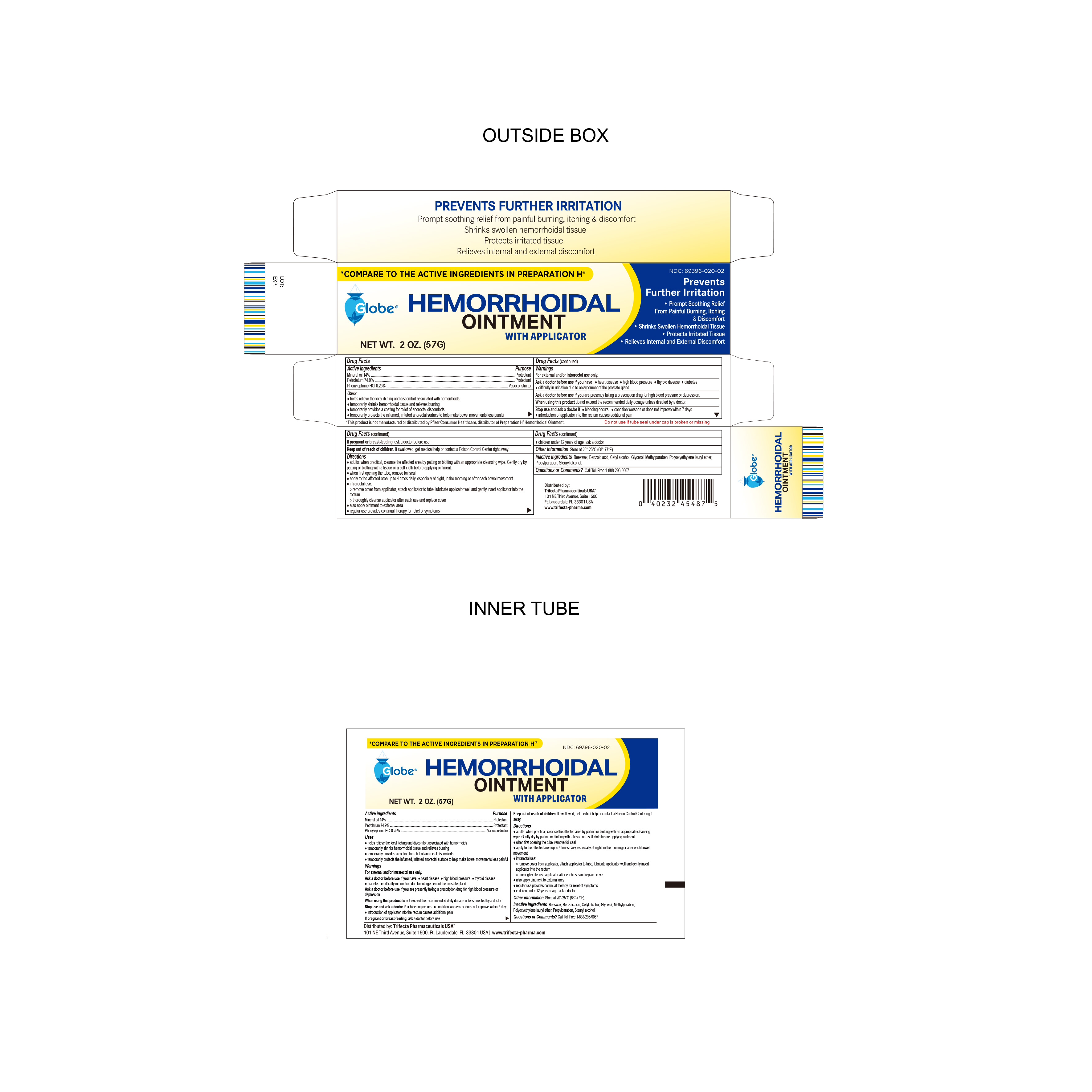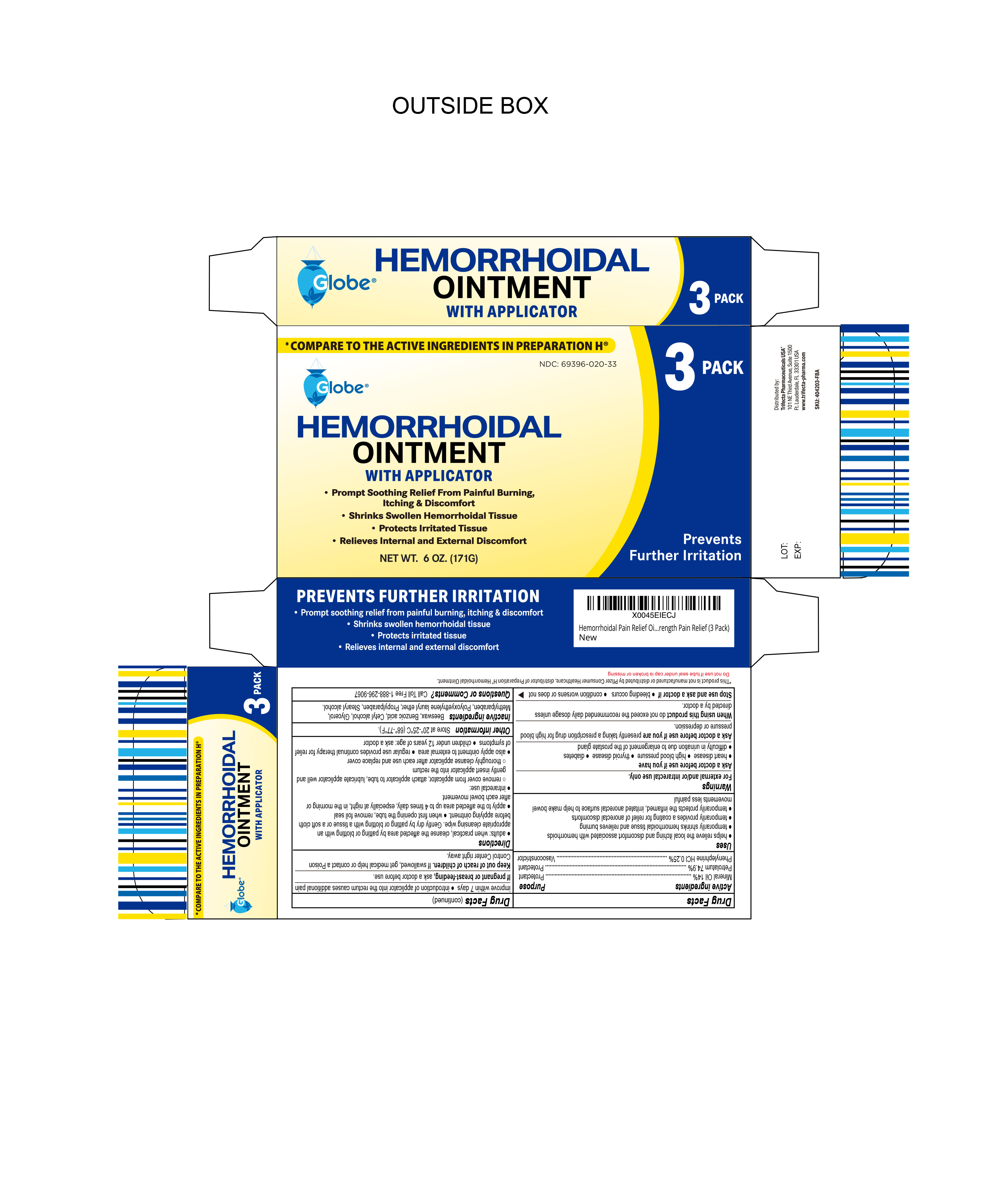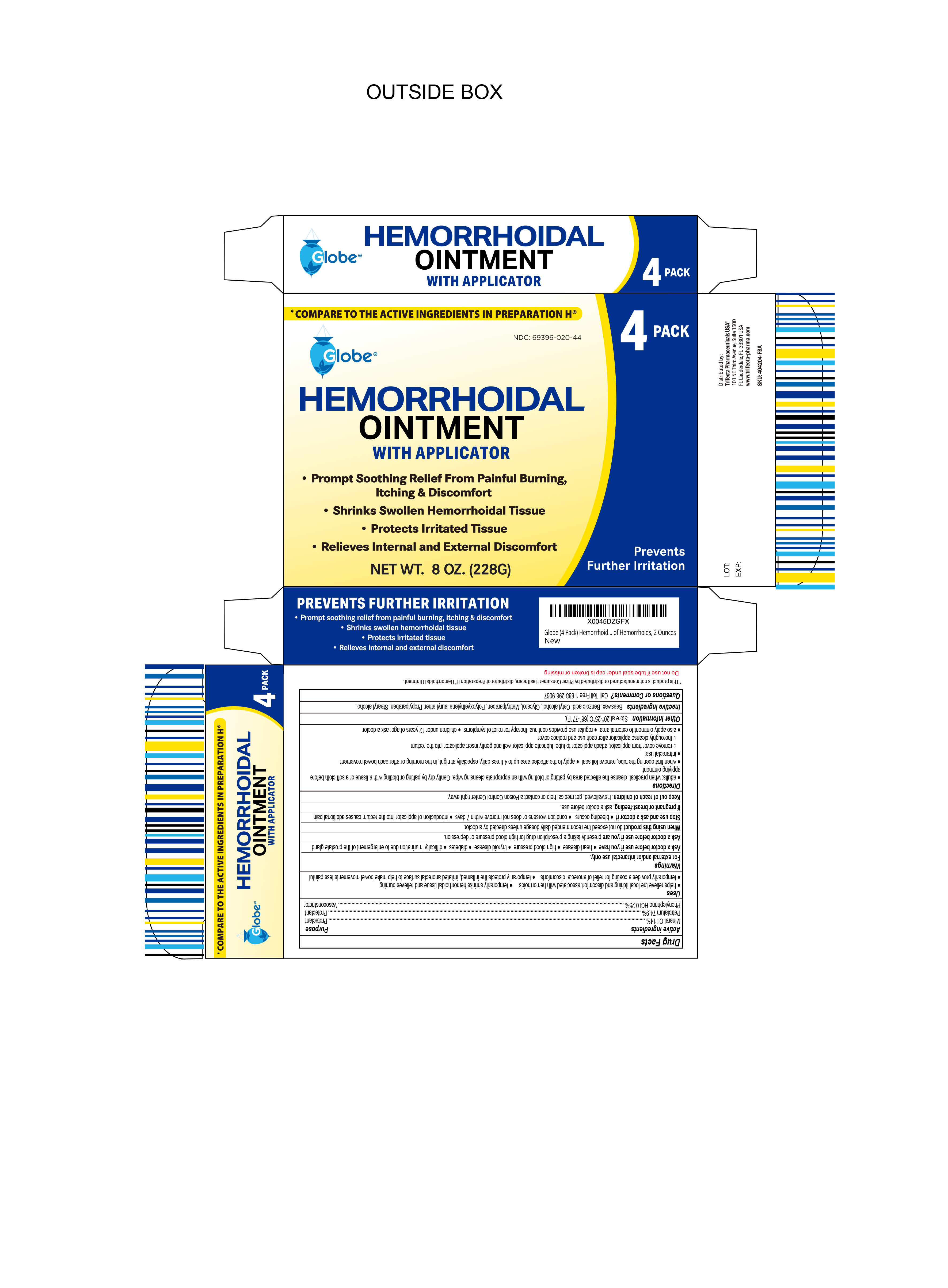 DRUG LABEL: HemorrhoidalOintment
NDC: 69396-020 | Form: OINTMENT
Manufacturer: Trifecta Pharmaceuticals USA LLC
Category: otc | Type: HUMAN OTC DRUG LABEL
Date: 20250609

ACTIVE INGREDIENTS: MINERAL OIL 14 g/100 g; PETROLATUM 74.9 g/100 g; PHENYLEPHRINE HYDROCHLORIDE 0.25 g/100 g
INACTIVE INGREDIENTS: CETYL ALCOHOL; BEESWAX; PROPYLPARABEN; METHYLPARABEN; GLYCERIN; BENZOIC ACID; LAURETH-23; STEARYL ALCOHOL

Hemorrhoidal Ointment

Active Ingredient

Phenylephrine HCI 0.25%

Purpose

Vasoconstrictor

Active Ingredient

Mineral Oil 14%

Purpose

Protectant

Active Ingredient

Petrolatum 74.9%

Purpose

Protectant

Uses

- Helps relieve the local itching and discomfort associated with hemorrhoids
- Temporarily shrinks hemorrhoidal tissue and relieves burning
- Temporarily provides a coating for relief of anorectal discomforts
- Temporarily profects the inflamed, irritated anorectal surface to help make bowel movements less painful

Warnings

For external and/or anorectal use only

Ask doctor before use if you have

- heart disease
- high blood pressure
- thyroid disease
- diabetes
- trouble urinating due to an enlarged prostate gland

Ask doctor before use if you are presently taking a prescription drug for high blood pressure

Stop Use and Ask Doctor if

- Bleeding occurs
- Condition worsens or does not improve within 7 days
- Introduction of applicator into the rectum causes additional pain

If Pregnant or Breast-Feeding

Ask a doctor before use

Keep out of reach of children

If swallowed get medical help or contact a Poison Control Center right away

Directions

Adults and children 12 years of age and older for topical use:

- Clean the affected area and pat or dab dry before applying ointment
- Apply to the affected area up to 4 times daily, especially after bowel movement
- Attach included applicator to tube
- Lubricate applicator tip and gently insert into rectum
- Thoroughly clean applicator after each use and replace cover

Children under 12 years of age: ask a doctor before use

Other Information

- Store at room temperature 20°-25°C (68°-77°F)
- Close cap tightly after use

Questions? Call 1-888-296-9067

Inactive Ingredients

Beeswax, Benzoic Acid, Cetyl alcohol, Glycerol Methylparaben, Polyoxyethylene lauryl ether, Propylparaben, Stearyl alcohol

Distributed By:

Trifecta Pharamceuticals USA, LLC.®

101 NE Third Ave. Suite 1500

Ft. Lauderdale, FL. 33301 USA

www.trifecta-pharma.com